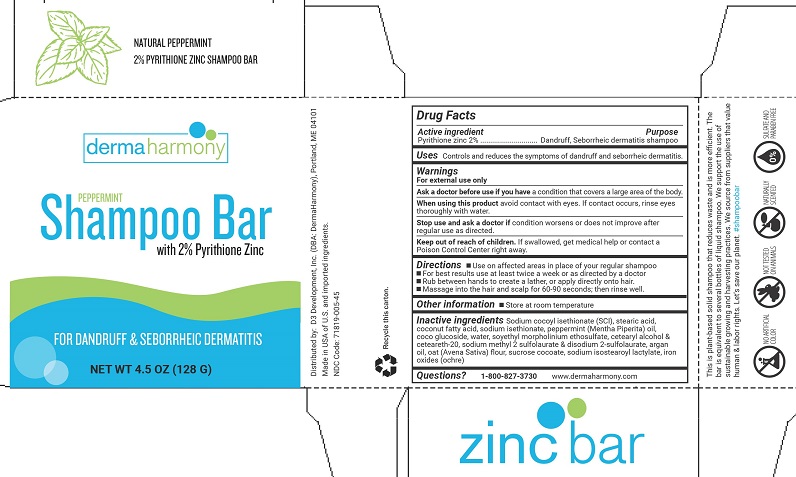 DRUG LABEL: Dermaharmony Bar
NDC: 71819-005 | Form: SHAMPOO
Manufacturer: D3 Development, Inc.
Category: otc | Type: HUMAN OTC DRUG LABEL
Date: 20241220

ACTIVE INGREDIENTS: PYRITHIONE ZINC 2 g/100 g
INACTIVE INGREDIENTS: BROWN IRON OXIDE; DISODIUM 2-SULFOLAURATE; OATMEAL; ARGAN OIL; WATER; SODIUM ISOSTEAROYL LACTYLATE; COCO GLUCOSIDE; SODIUM COCOYL ISETHIONATE; STEARIC ACID; COCONUT ACID; POLYOXYL 20 CETOSTEARYL ETHER; SOYETHYL MORPHOLINIUM ETHOSULFATE; CETOSTEARYL ALCOHOL; PEPPERMINT OIL; SODIUM METHYL 2-SULFOLAURATE; SODIUM ISETHIONATE; SUCROSE COCOATE

Dermaharmony Peppermint Shampoo Bar

Drug Facts

Active ingredient

Pyrithione zinc 2%

Purpose

Dandruff, Seborrheic dermatitis shampoo

Uses

Controls and reduces the symptoms of dandruff and seborrheic dermatitis.

Warnings

For external use only

Ask a doctor before use if you havea condition that covers a large area of the body.

WHEN USING

When using this productavoid contact with eyes. If contact occurs, rinse eyes thoroughly with water.

Stop use and ask a doctor ifcondition worsens or does not improve after regular use as directed.

Keep out of reach of children.If swallowed, get medical help or contact a Poison Control Center right away.

Directions

- Use on affected areas in place of your regular shampoo
- For best results use at least twice a week or as directed by a doctor
- Rub between hands to create a lather, or directly onto hair. Massage into the hair and scalp then rinse.

Other information

- Store at room temperature

Inactive ingredients

Sodium cocoyl isethionate (SCI), stearic acid, coconut fatty acid, sodium isethionate, peppermint (Mentha Piperita) oil, coco glucoside, water, soyethyl morpholinium ethosulfate, cetearyl alcohol & ceteareth-20, sodium methyl 2 sulfolaurate & disodium 2-sulfolaurate, argan oil, oat (Avena Sativa) flour, sucrose cocoate, sodium isostearoyl lactylate, iron oxides (ochre).

Questions?

1-800-827-3730

www.dermaharmony.com

Distributed by:

D3 Development, Inc. (DBA DermaHarmony), Portland, ME 04101

Made in USA of U.S. and imported ingredients.

NDC Code: 71819-005-45

PACKAGE LABEL

dermaharmony

PEPPERMINT

Shampoo Bar with 2% Pyrithione Zinc

FOR DANDRUFF & SEBORRHEIC DERMATITIS

NET WT 4.5 OZ (128 G)